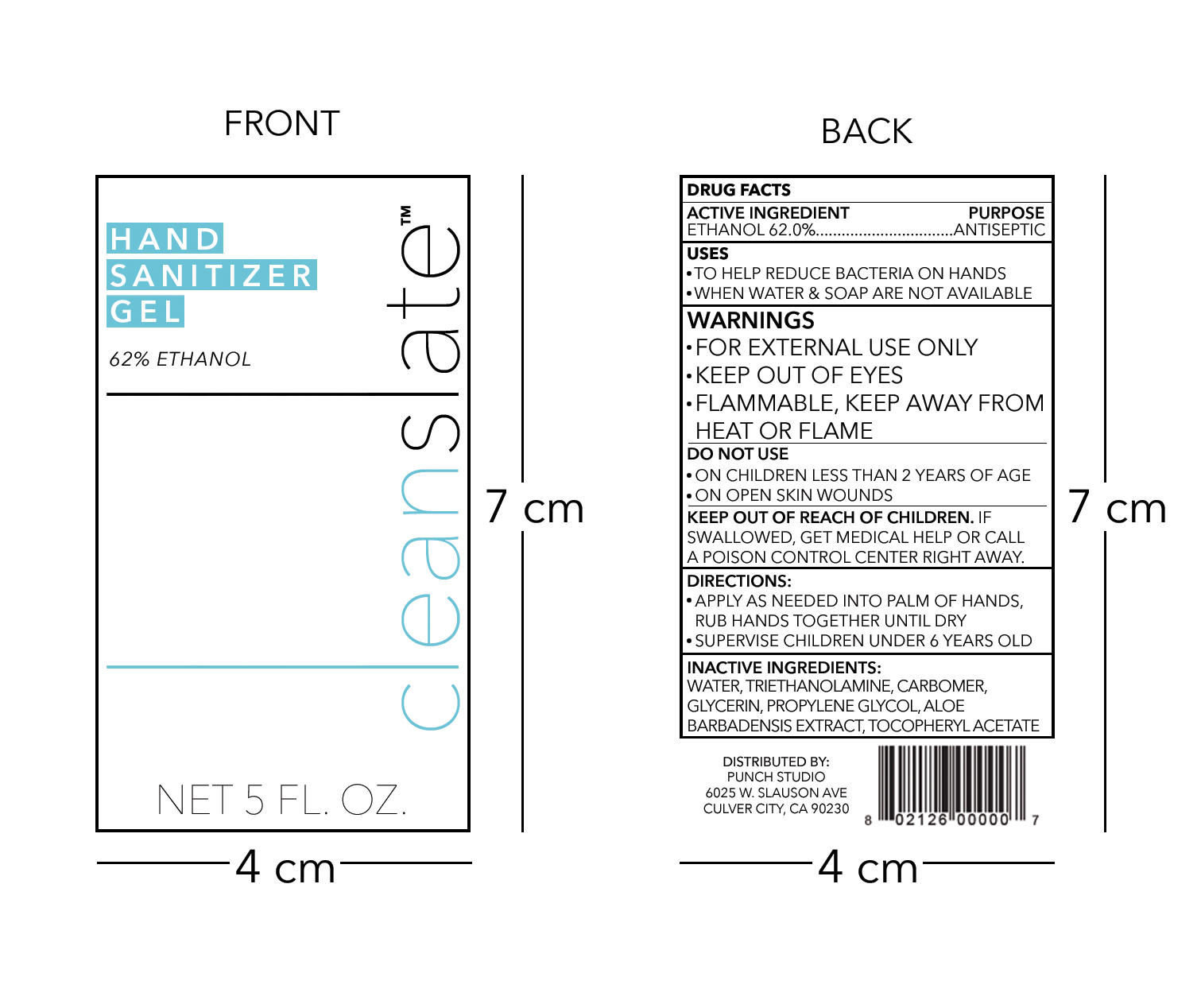 DRUG LABEL: Hand Sanitizer
NDC: 75601-0001 | Form: GEL
Manufacturer: Punch Studio, LLC
Category: otc | Type: HUMAN OTC DRUG LABEL
Date: 20220112

ACTIVE INGREDIENTS: ALCOHOL 93 mL/100 mL
INACTIVE INGREDIENTS: GLYCERIN 0.3 mL/100 mL; WATER 55.707 mL/100 mL; ALOE VERA LEAF 0.0015 mL/100 mL; ALPHA-TOCOPHEROL ACETATE 0.0015 mL/100 mL; PROPYLENE GLYCOL 0.15 mL/100 mL; CARBOMER HOMOPOLYMER, UNSPECIFIED TYPE 0.42 mL/100 mL; TROLAMINE 0.42 mL/100 mL

Hand sanitizer

ACTIVE INGREDIENT

EHTANOL 62%. PURPOSE: ANTISEPTIC

PURPOSE

ANTISEPTIC

USES

- TO HELP REDUCE BACTERIA ON HANDS
- WHEN WATER & SOAP ARE NOT AVAILABLE

WARNINGS

- FOR EXTERNAL USE ONLY
- KEEP OUT OF EYES
- FLAMMABLE, KEEP AWAY FROM HEAT OR FLAME

DO NOT USE

- ON CHILDREN LESS THAN 2 YEARS OF AGE
- ON OPEN SKIN WOUNDS

KEEP OUT OF REACK OF CHILDREN.

IF SWALLOWED, GET MEDICAL HELP OR CALL A POISON CONTROL VENTER RIGHT AWAY.

DIRECTIONS

- APPLY AS NEEDED INTO PALM OF HANDS, RUB HANDS TOGETHER UNTIL DRY
- SUPERVISE CHILDREN UNDER 6 YEARS OLD

INACTIVE INGREDIENTS

WATER, TRIETHANOLAMINE, CARBOMER, GLYCERIN, PROPYLENE GLYCOL, ALOE BARBADENSIS EXTRACT, TOCOPHERYL ACETATE

Package Label - Principal Display Panel

150 mL NDC: 75601-0001-1